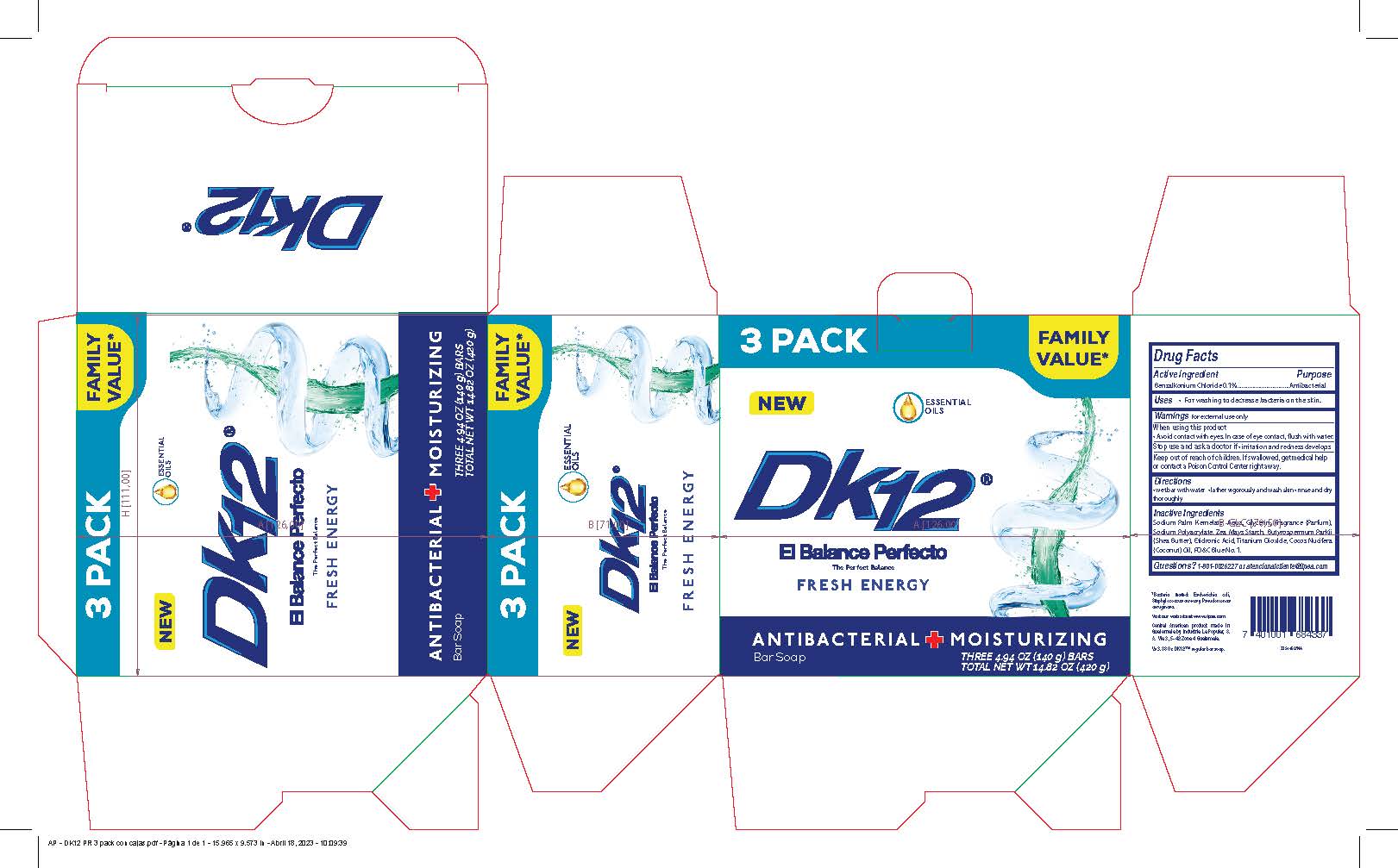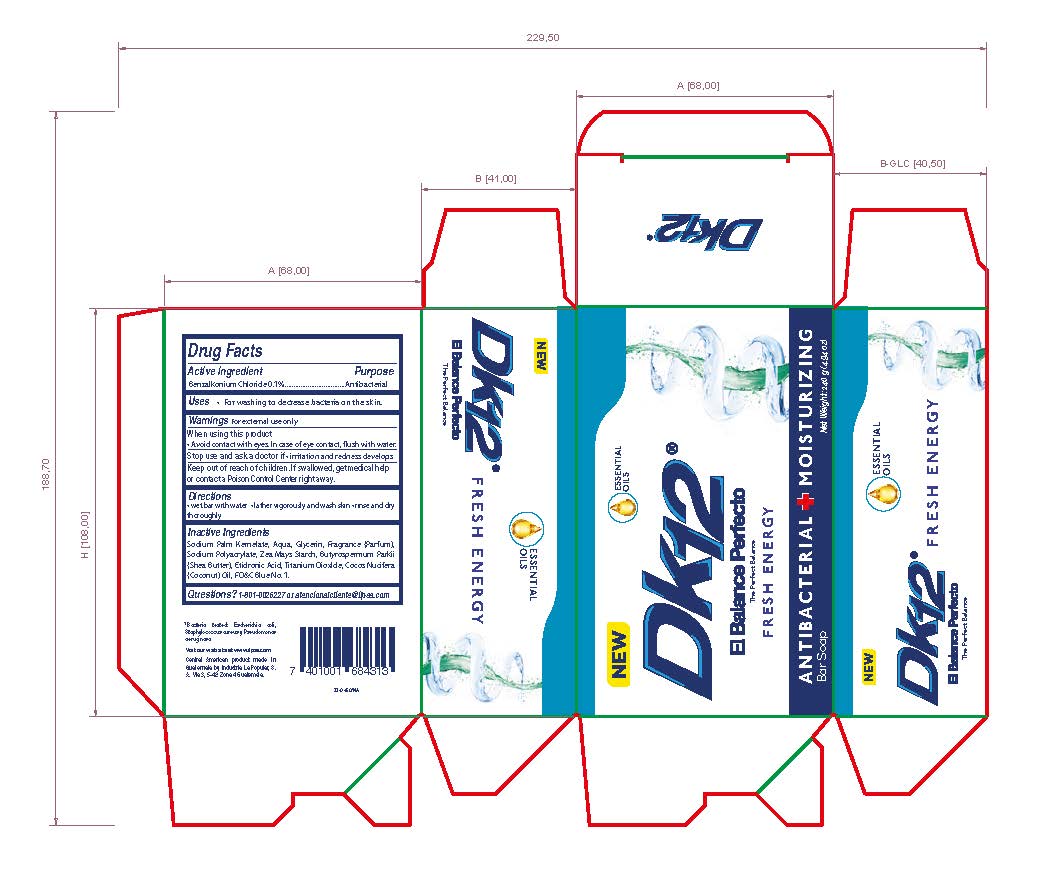 DRUG LABEL: DK12 Fresh Energy Antibacterial and Moisturizing
NDC: 62476-106 | Form: SOAP
Manufacturer: Industria La Popular, S.A.
Category: otc | Type: HUMAN OTC DRUG LABEL
Date: 20241202

ACTIVE INGREDIENTS: BENZALKONIUM CHLORIDE 0.1 g/110 g
INACTIVE INGREDIENTS: SODIUM PALM KERNELATE; GLYCERIN; WATER; TITANIUM DIOXIDE; SODIUM POLYACRYLATE (8000 MW); ETIDRONIC ACID; STARCH, CORN; BUTYROSPERMUM PARKII (SHEA) BUTTER UNSAPONIFIABLES; COCONUT OIL; FD&C BLUE NO. 1

DK12 Fresh Energy Bar Soap Antibacterial and Moisturizing

Active Ingredient

Benzalkonium Chloride 0.1%

Purpose

Antibacterial

Uses

For washing to decrease bacteria on the skin.

Warnings

For External Use only.

When using this product

Avoid contact with eyes. In case of eye contact, flush with water.

Stop use and ask a doctor

If irritation and redness develops

Keep out of reach of children.

If swallowed, get medical help or contact a Poison Control Center right away.

Directions

Wet bar with water
Lather vigorously and wash skin

Rinse and dry thoroughly

Inactive Ingredients

Sodium Palm Kernelate, Water, Glycerin, Fragrance (Perfume), Sodium Polyacrylate, Zea May Starch, Butyrospermum Parkii (Shea Butter), Etidronic Acid, Titanium Dioxide, Cocos Nucitera (coconut) oil, FD&C Blue No. 1.

Questions

1-801-0026227 or atencionalcliente@ilpsa.com